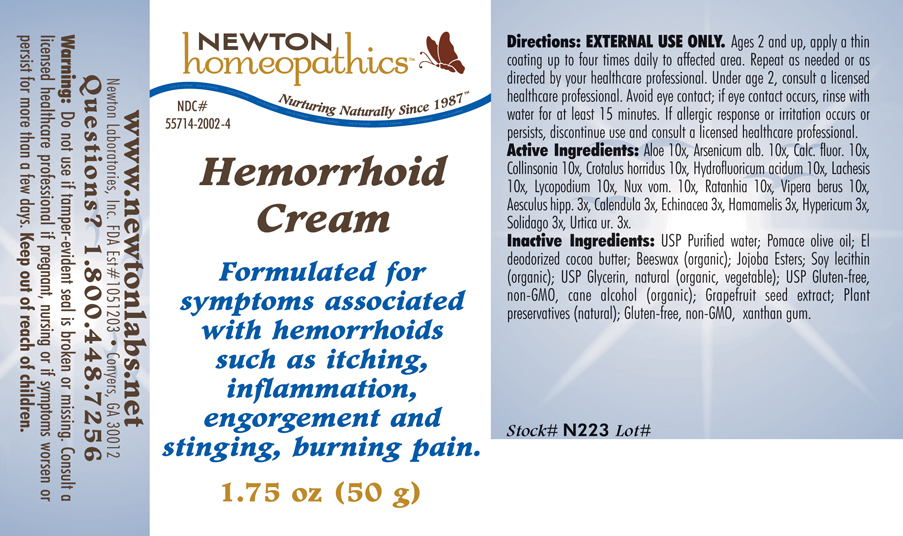 DRUG LABEL: Hemorrhoid Cream 
NDC: 55714-2002 | Form: CREAM
Manufacturer: Newton Laboratories, Inc.
Category: homeopathic | Type: HUMAN OTC DRUG LABEL
Date: 20130801

ACTIVE INGREDIENTS: Aloe 10 [hp_X]/1 g; Arsenic Trioxide 10 [hp_X]/1 g; Calcium Fluoride 10 [hp_X]/1 g; Collinsonia Canadensis Root 10 [hp_X]/1 g; Crotalus Horridus Horridus Venom 10 [hp_X]/1 g; Hydrofluoric Acid 10 [hp_X]/1 g; Lachesis Muta Venom 10 [hp_X]/1 g; Lycopodium Clavatum Spore 10 [hp_X]/1 g; Strychnos Nux-vomica Seed 10 [hp_X]/1 g; Krameria Lappacea Root 10 [hp_X]/1 g; Vipera Berus Venom 10 [hp_X]/1 g; Horse Chestnut 3 [hp_X]/1 g; Calendula Officinalis Flowering Top 3 [hp_X]/1 g; Echinacea, Unspecified 3 [hp_X]/1 g; Hamamelis Virginiana Root Bark/stem Bark 3 [hp_X]/1 g; Hypericum Perforatum 3 [hp_X]/1 g; Solidago Virgaurea Flowering Top 3 [hp_X]/1 g; Urtica Urens 3 [hp_X]/1 g
INACTIVE INGREDIENTS: Water; Olive Oil; Cocoa Butter; Royal Jelly; Jojoba Oil; Lecithin, Soybean; Glycerin; Alcohol; Citrus Paradisi Seed; Lonicera Japonica Flower; Xanthan Gum

Hemorrhoid Cream

INDICATIONS & USAGE SECTION

Hemorrhoid Cream: Formulated for symptoms associated with hemorrhoids such as itching, inflammation, engorgement and stinging, burning pain.

DOSAGE & ADMINISTRATION SECTION

Directions: EXTERNAL USE ONLY. Ages 2 and up, apply a thin coating up to four times daily to affected area. Repeat as needed or as directed by your healthcare professional. Under age 2, consult a licensed healthcare professional. Avoid eye contact; if eye contact occurs, rinse with water for at least 15 minutes. If allergic response or irritation occurs or persists, discontinue use and consult a licensed healthcare professional.

OTC - ACTIVE INGREDIENT SECTION

Aloe 10x, Arsenicum alb. 10x, Calc. fluor. 10x, Collinsonia 10x, Crotalus horridus 10x, Hydrofluoricum acidum 10x, Lachesis 10x, Lycopodium 10x, Nux vom. 10x, Ratanhia 10x, Vipera berus 10x, Aesculus hipp. 3x, Calendula 3x, Echinacea 3x, Hamamelis 3x, Hypericum 3x, Solidago 3x, Urtica ur. 3x.

INACTIVE INGREDIENT SECTION

USP Purified Water, Pomace Olive Oil, El Deodorized Cocoa Butter, Beeswax (organic), Jojoba Esters, Soy Lecithin (organic), USP Glycerin, natural (organic, vegetable), USP Gluten-free, non-GMO, Cane Alcohol (organic), Grapefruit Seed Extract, Plant preservatives (natural), Gluten-free, non-GMO, Xanthan Gum.

OTC - QUESTIONS SECTION

www.newtonlabs.net Newton Laboratories, Inc. FDA Est # 1051203 - Conyers, GA 30012 Questions? 1.800.448.7256

WARNINGS SECTION

Warning: Do not use if tamper - evident seal is broken or missing. Consult a licensed healthcare professional if pregnant, nursing or if symptoms worsen or persist for more than a few days. Keep out of reach of children.

OTC - PREGNANCY OR BREAST FEEDING SECTION

Consult a licensed healthcare professional if pregnant, nursing or if symptoms worsen or persist for more than a few days.

OTC - KEEP OUT OF REACH OF CHILDREN SECTION

Keep out of reach of children.